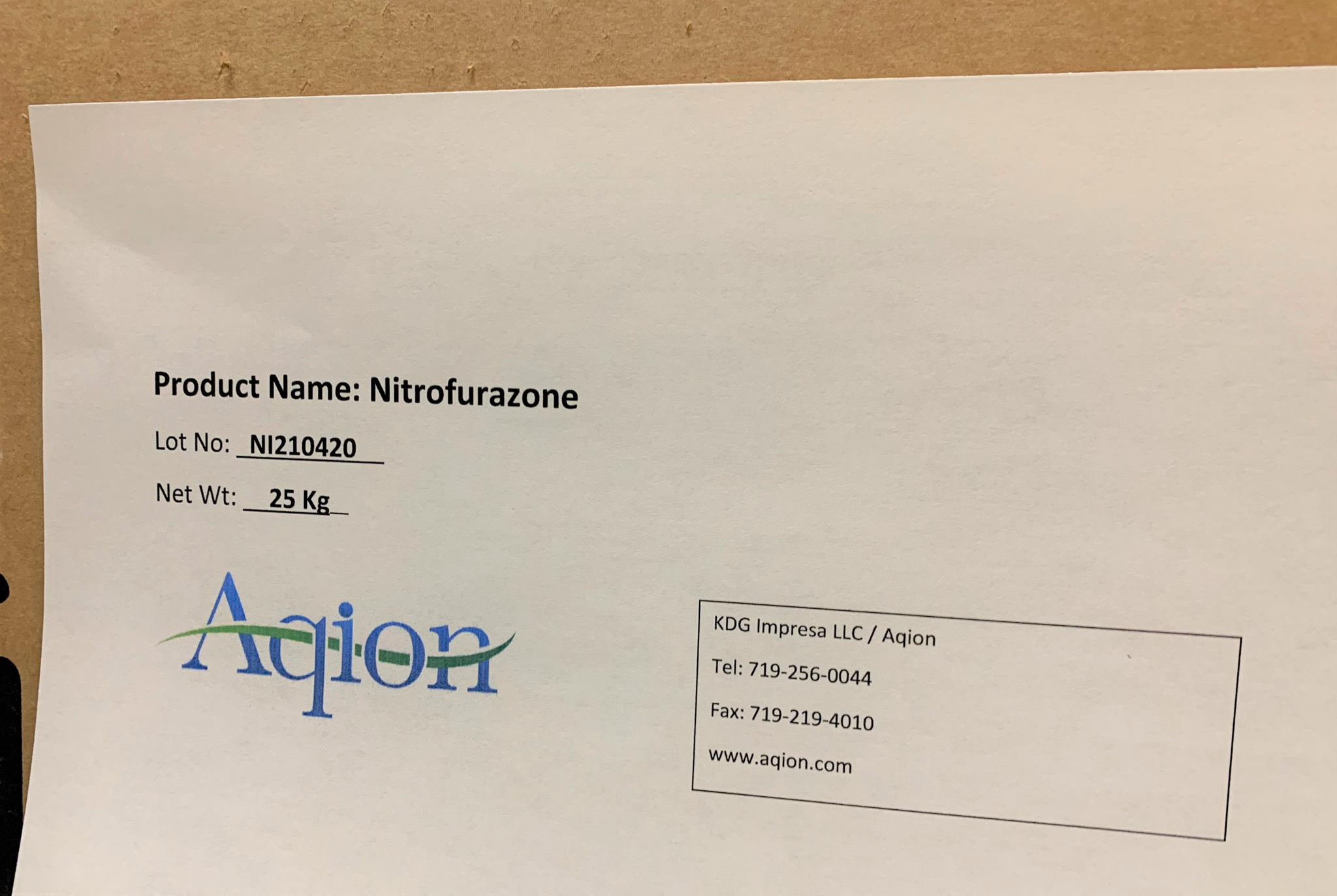 DRUG LABEL: Nitrofurazone
NDC: 43457-648 | Form: POWDER
Manufacturer: KDG Impresa LLC, Aqion
Category: other | Type: BULK INGREDIENT - ANIMAL DRUG
Date: 20220218

ACTIVE INGREDIENTS: NITROFURAZONE 1 kg/1 kg

Nitrofurazone